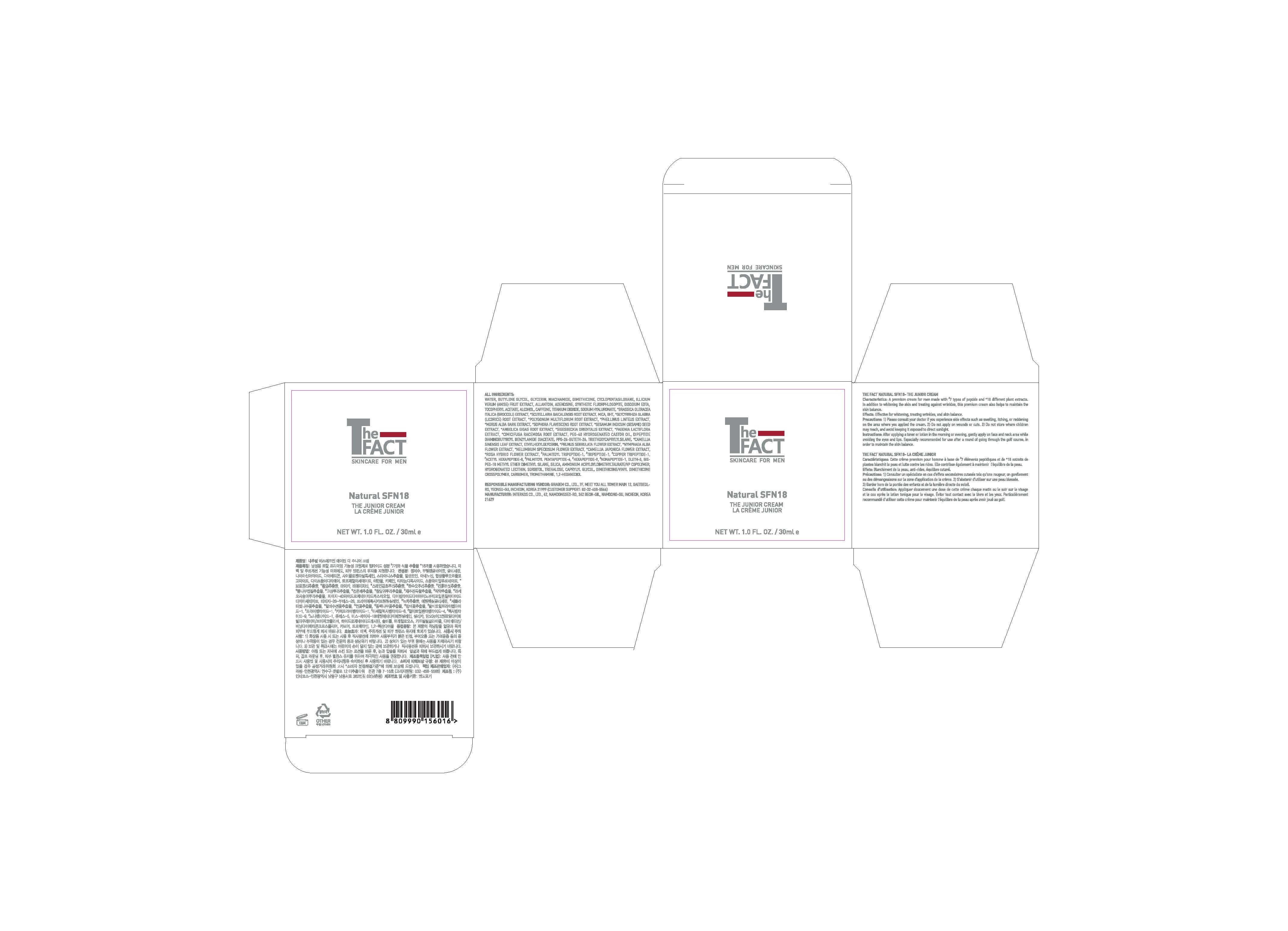 DRUG LABEL: The Fact Natural SPN18 - The JuniorCream
NDC: 77049-0002 | Form: CREAM
Manufacturer: Interkos Co.,Ltd.
Category: otc | Type: HUMAN OTC DRUG LABEL
Date: 20200503

ACTIVE INGREDIENTS: NIACINAMIDE 3 g/100 mL; ADENOSINE 0.04 g/100 mL
INACTIVE INGREDIENTS: BUTYLENE GLYCOL; GLYCERIN

Drug Facts

ACTIVE INGREDIENT

niacinamide, adenosine

INACTIVE INGREDIENT

water, butylene glycol, glycerin, dimethicone, cyclopentasiloxane, illicium verum(anise) fruit extract, allantoin, synthetic fluorphlogopite, disodium edta, tocopheryl acetate, alcohol, caffeine, titanuim dioxide, sodium hyaluronate, brassica oleracea italica (broccoli) extract, scutellaria baicalensis root extract, mica, bht, glycyrrhiza glabra (licorice) root extract, polygonum multiflorum root extract, phellinus linteus extract, morus alba bark extract, sophora flavescens root extract, sesamum indicum (sesame) seed extract, angelica gigas root extract, sigesbeckia orientalis extract, paeonia lactiflora extract, cimicifuga racemosa root extract, peg-40 hydrogenated castor oil, dipeptide diaminobutyroyl benzylamide diacetate, ppg-26-buteth-26, triethoxycaprylylsilane, camellia sinensis leaf extract, ethylhexylglycerin, prunus serrulata flower extract, nymphaea alba flower extract, nelumbium speciosum flower extract, camellia japonica flower extract, rosa hybrid flower extract, palmitoyl tripeptide-1, tripeptide-1, copper tripeptide-1, acetyl hexapeptide-8, palmitoyl pentapeptide-4, hexapeptide-9, nonapeptide-1, oleth-5, bis-peg18 methyl ether dimethyl silane, silica, ammonium acryloyldimethyltaurate/vp copolymer, hydrogenated lecithin, sorbitol, trehalose, caprylyl glycol, dimethicone/vinyl dimethicone crosspolymer, carbomer, tromethamine, 1,2-hexanediol

PURPOSE

for skin protectant

KEEP OUT OF REACH OF THE CHILDREN

INDICATIONS AND USAGE

After applying a toner or lotion in the morning or evening, gently apply on face and neck area while avoiding the eyes and lips. Especially recommended for use after a round of going through the golf course, in order to maintain the skin balance.

WARNINGS

1) Please consult your doctor if you experience side effects such as swelling, itching, or reddening on the area where you applied the cream.

2) Do not apply on wounds or cuts. 3) Do not store where children may reach, and avoid keeping it exposed to direct sunlight.

DOSAGE AND ADMINISTRATION

external use only